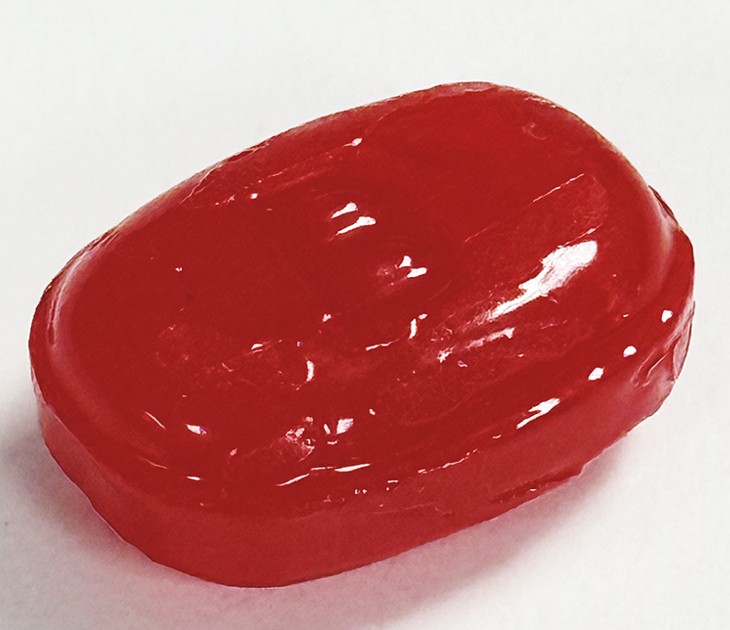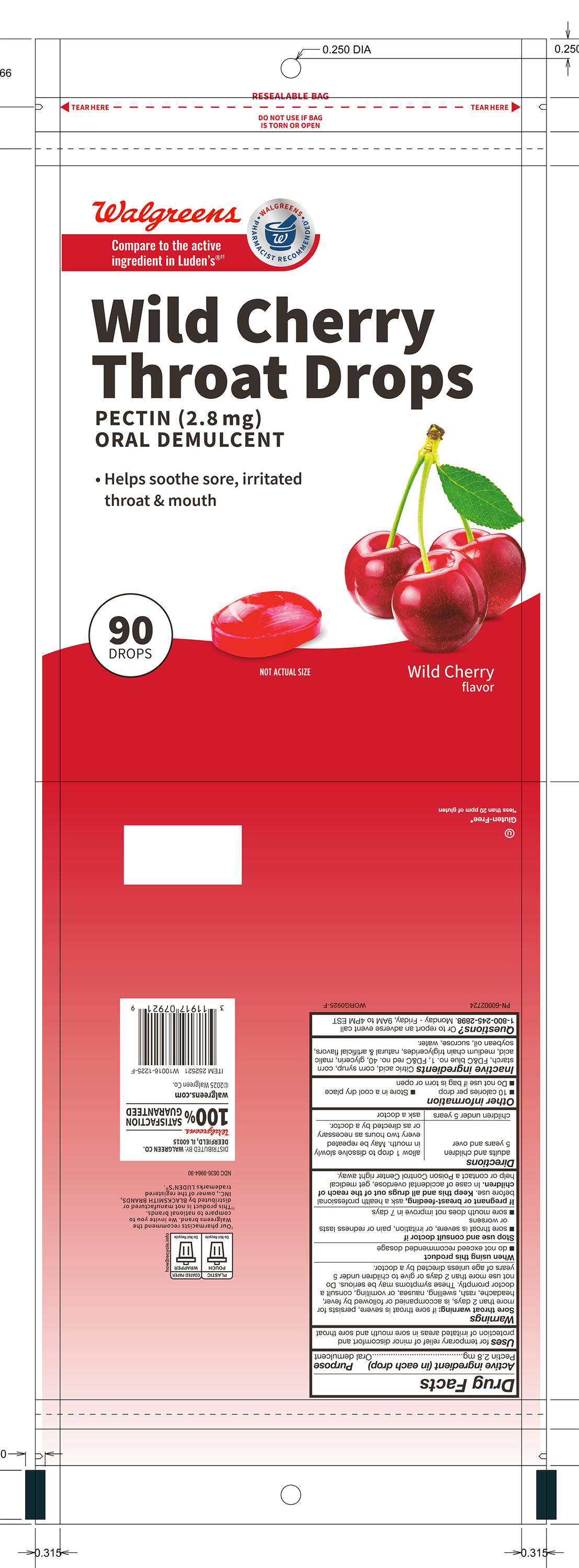 DRUG LABEL: Walgreens Wild Cherry Pectin Throat Drops
NDC: 0363-9964 | Form: LOZENGE
Manufacturer: Walgreens
Category: otc | Type: HUMAN OTC DRUG LABEL
Date: 20260218

ACTIVE INGREDIENTS: PECTIN 2.8 mg/1 1
INACTIVE INGREDIENTS: WATER

Pectin 2.8 mg

Active ingredient (in each drop)

Pectin 2.8 mg

Purpose

Oral demulcent

INDICATIONS AND USAGE

Uses for temporary relief of minor discomfort and protection of irritated areas in sore mouth and sore throat

Warnings

Sore throat warning: if sore throat is severe, persists for more than 2 days, is accompanied or followed by fever, headache, rash, swelling, nausea, or vomiting, consult a doctor promptly. These symptoms may be serious. Do not use more than 2 days or give to children under 5 years of age unless directed by a doctor,

When using this product

- do not exceed recommended dosage

Stop use and consult doctor if

- sore throat is severe, or irritation, pain or redness lasts or worsens
- sore mouth does not improve in 7 days

PREGNANCY OR BREAST FEEDING

If pregnant or breast-feeding, ask a health professional before use.

KEEP OUT OF REACH OF CHILDREN

Keep this and all drugs out of the reach of children.

OVERDOSAGE

In case of accidental overdose, get medical help or contact a Poison Control Center right away.

Directions

adults and children 5 years and over - allow 1 drop to dissolve slowly in mouth. May be repeated every two hours as necessary or as directed by a doctor.

children under 5 years - ask a doctor

Other information

- 10 calories per drop
- Store in a cool dry place
- Do not use if bag is torn or open

INACTIVE INGREDIENT

Inactive ingredients: Citric acid, corn syrup, corn starch, FD&C blue no. 1, FD&C red no. 40, glycerin malic acid, medium chain triglycerides, natural and artificial flavors, soybean oil, sucrose, water.

QUESTIONS

Questions? Or to report an adverse event call 1-800-245-2898. Monday - Friday, 9AM to 4PM EST